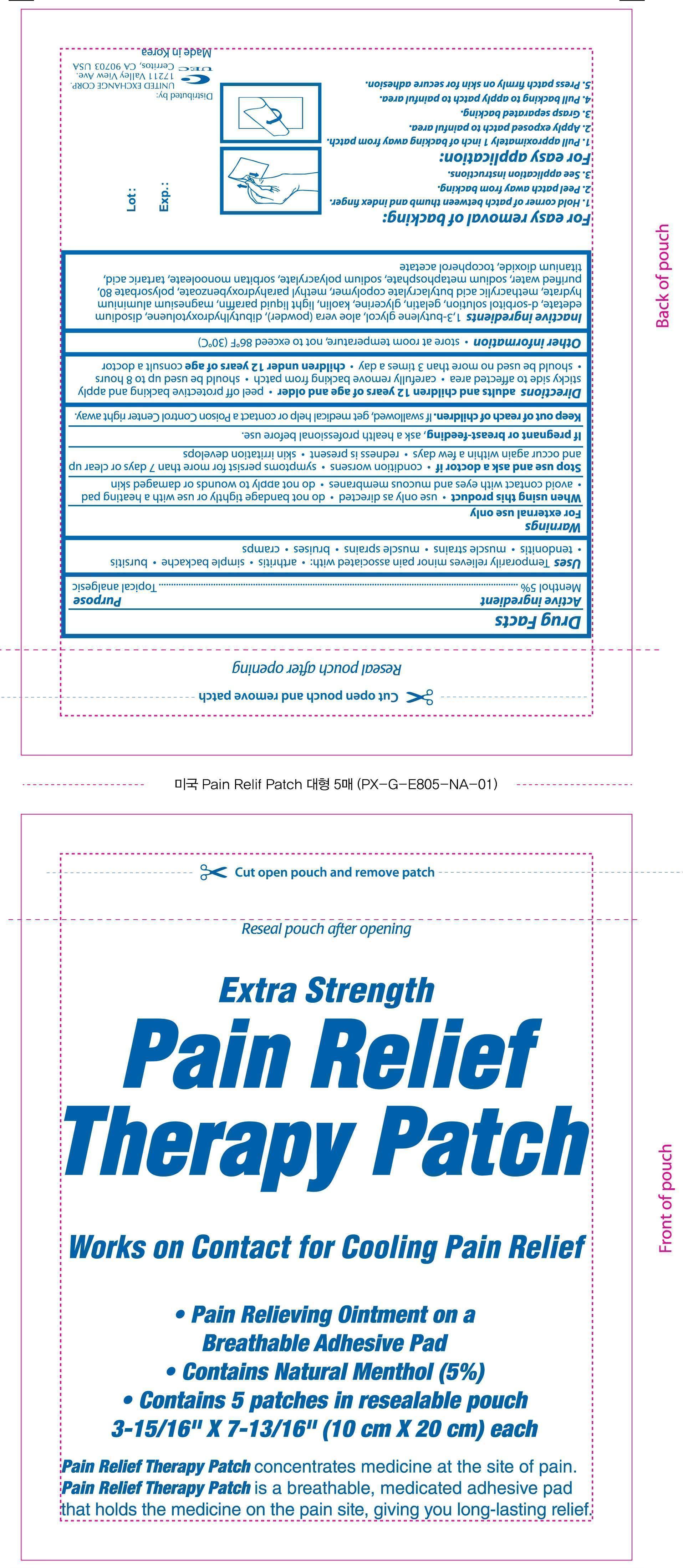 DRUG LABEL: Extra Strength Pain Relief Therapy
NDC: 65923-704 | Form: PATCH
Manufacturer: United Exchange Corp
Category: otc | Type: HUMAN OTC DRUG LABEL
Date: 20140828

ACTIVE INGREDIENTS: MENTHOL 750 mg/1 1
INACTIVE INGREDIENTS: ALOE VERA LEAF; ALUMINUM HYDROXIDE; BUTYLATED HYDROXYTOLUENE; CASTOR OIL; EDETATE DISODIUM; GELATIN; GLYCERIN; ISOPROPYL MYRISTATE; KAOLIN; METHYLPARABEN; PEG-40 STEARATE; POLYSORBATE 80; POLYVINYL ALCOHOL; WATER; TARTARIC ACID; TITANIUM DIOXIDE; ALPHA-TOCOPHEROL ACETATE

Active ingredient Purpose

Menthol 5%................................................................................Topical analgesic

PURPOSE

Uses Temporarily relieves minor pain associated with:

- arthritis
- simple backache
- bursitis
- tendonitis
- muscle strains
- muscle sprains
- bruises
- cramps

Warnings For external use only.

When using this product

- use only as directed
- do not bandage tightly or use with a heating pad
- avoid contact with eyes and mucous membranes
- do not apply to wounds or damaged skin

Stop use and ask a doctor if

- condition worsens
- symptoms persist for more than 7 days or clear up and occur again within a few days
- redness is present
- skin irritation develops

Keep out of reach of children. If swallowed, get medical help or contact a Poison Control Center right away.

PREGNANCY OR BREAST FEEDING

If pregnant or breast-feeding, ask a health professional before use.

Directions

- adults and children 12 years of age and older
- peel off protective backing and apply sticky side to affected area
- carefully remove backing from patch
- should be used up to 8 hours should be used no more than 3 times a day
- children under 12 years of age consult a doctor

Other information

- store at room temperature, not to exceed 86°F (30°C)

INACTIVE INGREDIENT

Inactive ingredients aloe barbadenisis leaf juice, aluminum hydroxide, BHT, castor oil, disodium edetate, gelatin, glycerin, isopropyl myristate, kaolin, magnesium aluminate metasilicate, methyl paraben, peg-40 stearate, polysorbate 80, polyvinyl alcohol, purified water, PVP sodium polyacrylate, tartaric acid, titanium dioxide, tocopherol acetate, Release Liner: polypropylene, Non-Woven Material: Polyester Non-Woven Fabric.

DOSAGE AND ADMINISTRATION

Distributed By:

United Exchange Corp

17211 Valley View Ave.

Cerritos, CA 90703 USA

Made in Korea